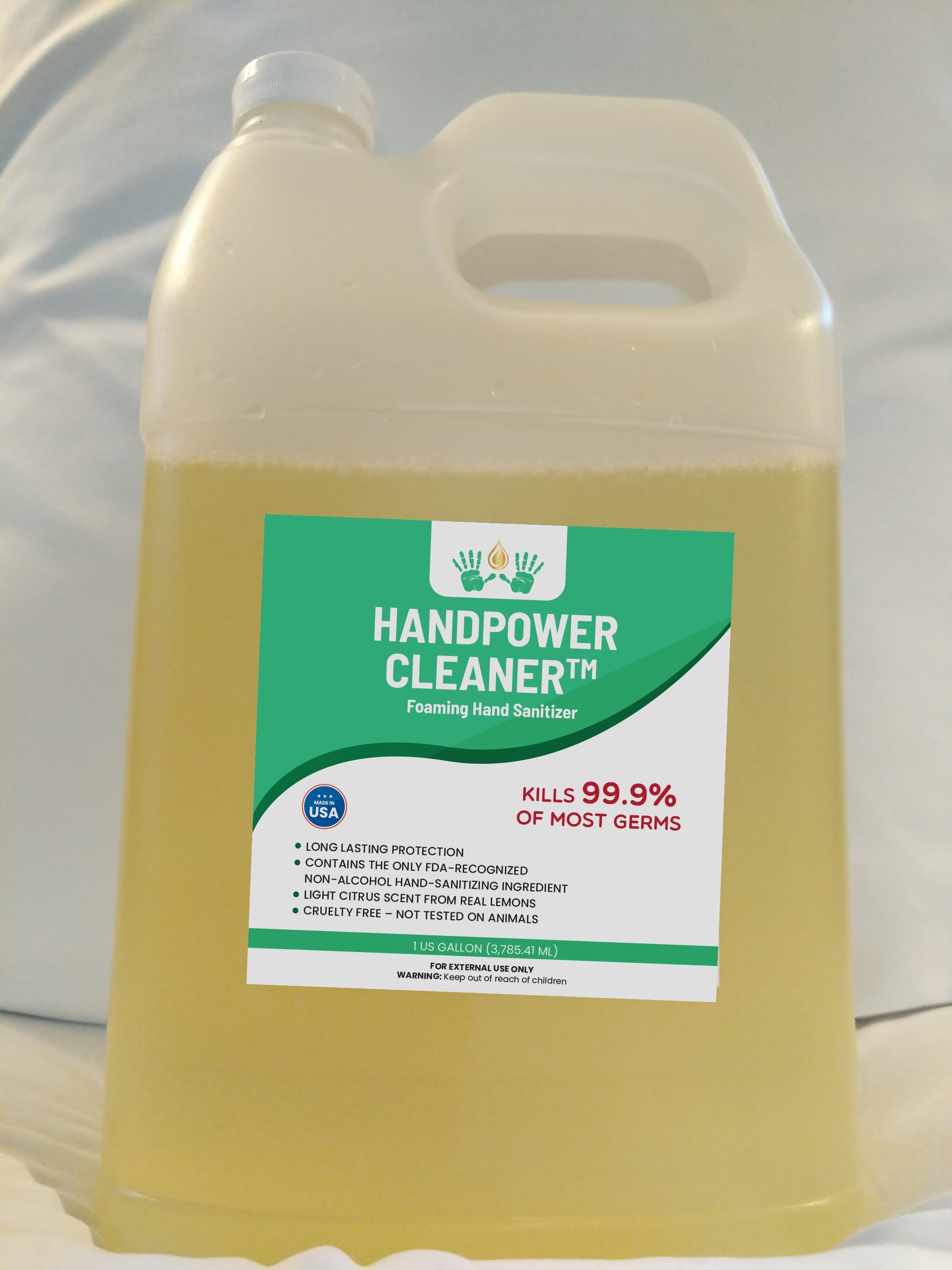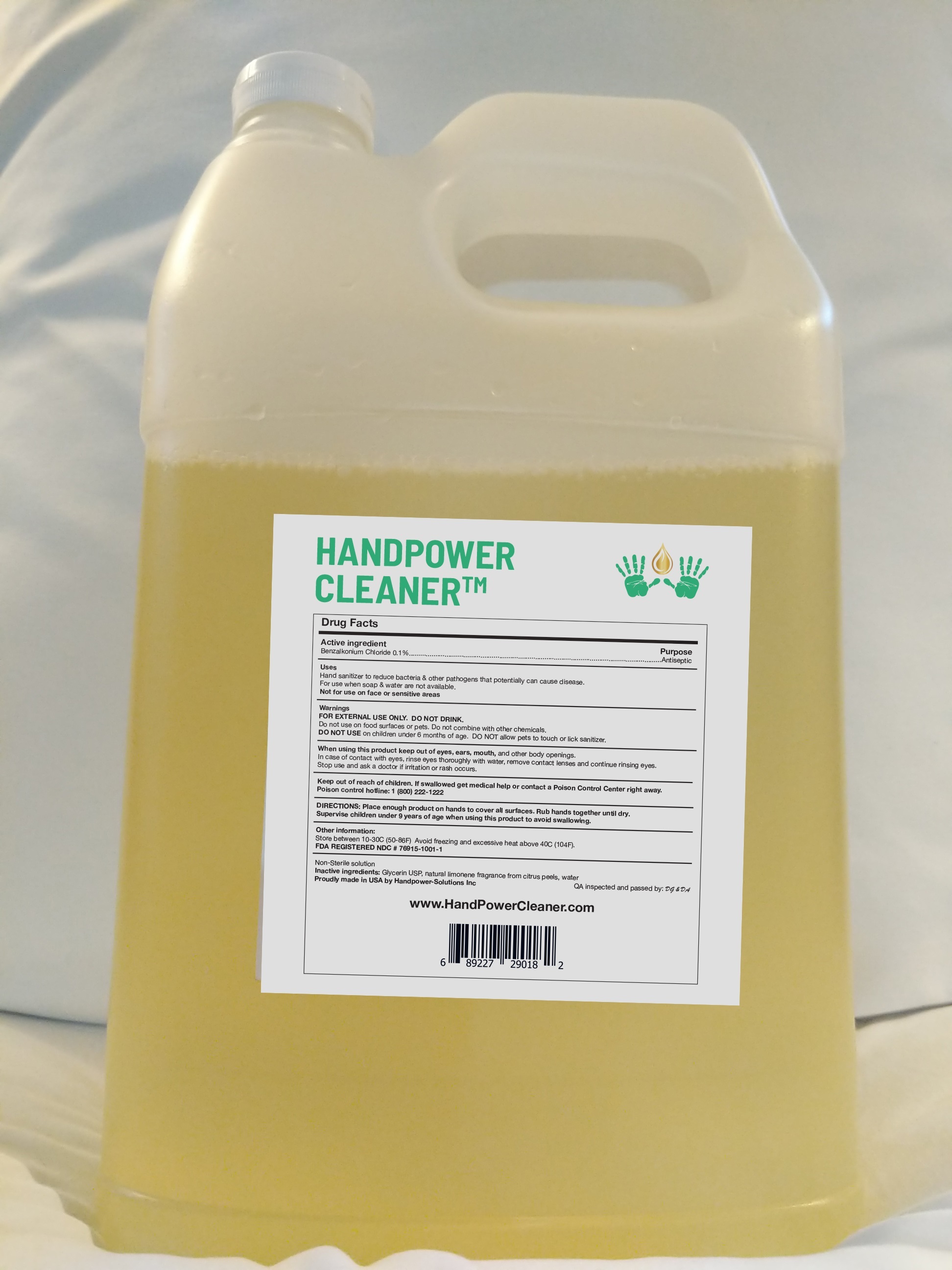 DRUG LABEL: HANDPOWER CLEANER (TM) Hand Sanitizer
NDC: 76915-1001 | Form: LIQUID
Manufacturer: handpower solutions inc
Category: otc | Type: HUMAN OTC DRUG LABEL
Date: 20211231

ACTIVE INGREDIENTS: BENZALKONIUM CHLORIDE 1 mg/1 mL
INACTIVE INGREDIENTS: GLYCERIN 0.0025 mL/1 mL; LEMON OIL, DISTILLED 0.004 mL/1 mL

Handpower Cleaner (TM) Hand Sanitizer

Active Ingredient

Active Ingredient_____________________________________Purpose

Benzalkonium Chloride 0.1% ………………………………..……... Antiseptic

Purpose

Active Ingredient_____________________________________Purpose

Benzalkonium Chloride 0.1% ………………………………..……... Antiseptic

Uses.

Uses: Hand sanitizer to help reduce bacteria and other pathogens that potentially can cause disease. For use when soap and water are not available. Not for use on the face or other sensitive areas.

Warnings:

Warnings: FOR EXTERNAL USE ONLY. DO NOT DRINK. Do not use on food surfaces or pets. Do not combine with other chemicals.

DO NOT USE on children less than 6 months of age.

When using this product

When using this productkeep out of eyes, ears, mouth, and other body openings. In case of contact with eyes, rinse eyes thoroughly with water, remove contact lenses and continue rinsing eyes.

Stop use

Stop use and ask a doctor if irritation or rash occurs.

Keep out of reach of children. If swallowed get medical help or contact a Poison Control Center right away.

Poison control hotline: 1 (800) 222-1222

Directions:

Directions: Place enough product on hands to cover all surfaces. Rub hands together until dry. Supervise children under 9 years of age when using this product to avoid swallowing.

Other information:

Other information: Store between 10-30C (50-86F)
Avoid freezing and excessive heat above 40C (104F)

Inactive ingredients:

Non-Sterile solution

Inactive ingredients: Glycerin USP, natural fragrance from citrus peels, water

FDA REGISTERED NDC # 76915-1001-1

Part of bottom of rear label

Proudly made in USA by Handpower Solutions Inc QA inspected and passed by: DG & DA

www.HandPowerCleaner.com

(UPC bar code 6 89227 29018 2)